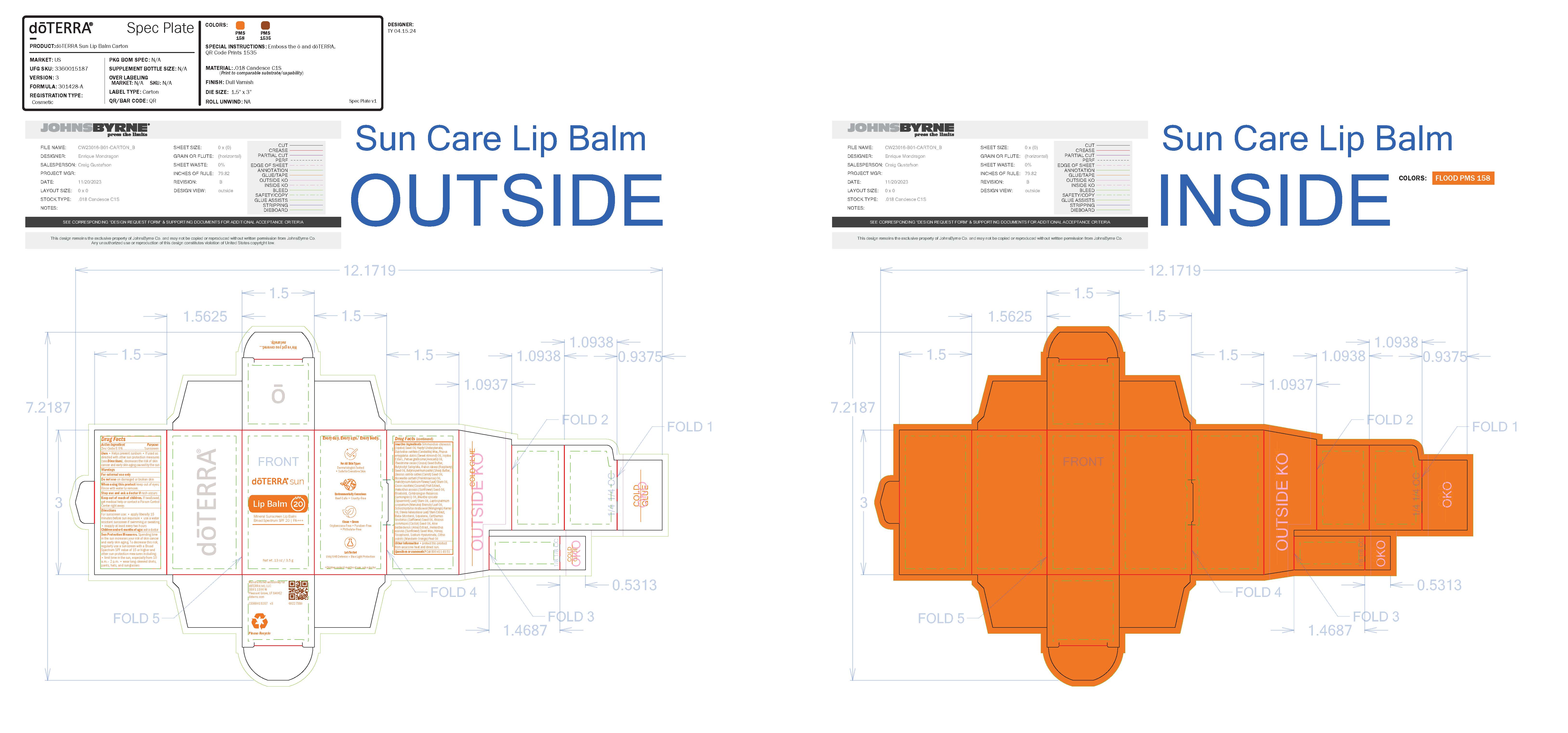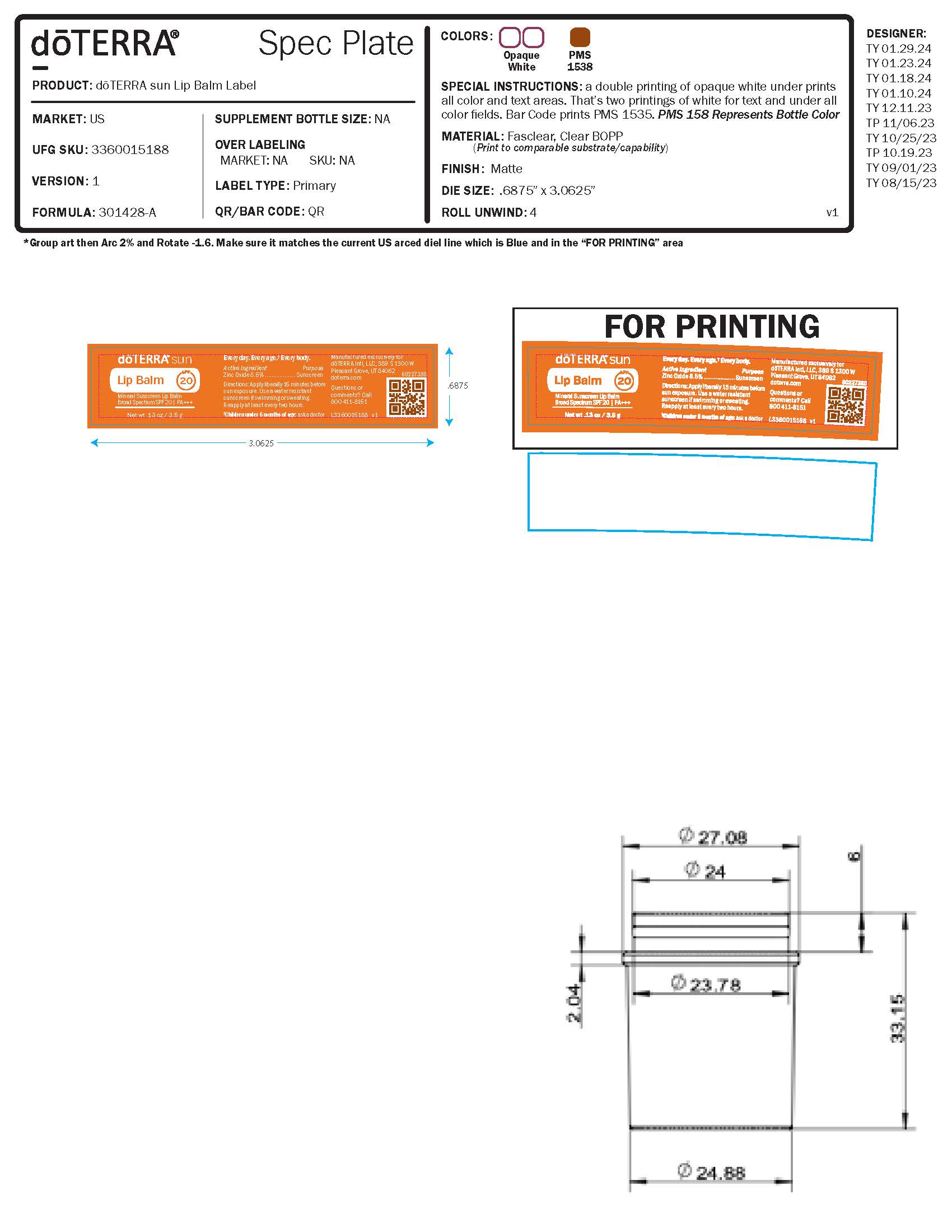 DRUG LABEL: doTERRA sun Lip Balm Mineral Sunscreen
NDC: 71630-116 | Form: STICK
Manufacturer: doTERRA International, LLC
Category: otc | Type: HUMAN OTC DRUG LABEL
Date: 20240827

ACTIVE INGREDIENTS: ZINC OXIDE 8.7 g/100 g
INACTIVE INGREDIENTS: .BETA.-BISABOLOL; PEG-9 DIGLYCIDYL ETHER/SODIUM HYALURONATE CROSSPOLYMER; ALOE VERA WHOLE; CITRUS NOBILIS; COCOS NUCIFERA WHOLE; LEPTOSPERMUM SCOPARIUM WHOLE; BUTYLOCTANOL; ALMOND OIL; TOCOPHEROL; CANDELILLA WAX; SODIUM BETA-SITOSTERYL SULFATE; HELIANTHUS ANNUUS WHOLE; HELIANTHUS ANNUUS SEED WAX; CARTHAMUS TINCTORIUS WHOLE; BUTYROSPERMUM PARKII (SHEA) BUTTER UNSAPONIFIABLES; AVOCADO OIL; RICINUS COMMUNIS SEED; MENTHA SPICATA OIL; COCOA BUTTER; SCHINZIOPHYTON RAUTANENII WHOLE; HELICHRYSUM ITALICUM WHOLE; SIMMONDSIA CHINENSIS SEED; STEVIA REBAUDIANA LEAF; BOSWELLIA SERRATA RESIN OIL; POTASSIUM HYDROLYZED JOJOBA ESTERS; CARROT SEED OIL; HONEY; CYMBOPOGON FLEXUOSUS WHOLE; HEPTYL UNDECYLENATE; BUTYLOCTYL SALICYLATE; RUBUS IDAEUS SEED; SQUALENE

Active Ingredient Purpose
Zinc Oxide 8.5% ........................Sunscreen

PURPOSE

Sunscreen

INDICATIONS AND USAGE

Uses • Helps prevent sunburn • If used as
directed with other sun protection measures
(see Directions), decreases the risk of skin
cancer and early skin aging caused by the sun

Warnings
For external use only
Do not use on damaged or broken skin
When using this product keep out of eyes.
Rinse with water to remove.
Stop use and ask a doctor if rash occurs
Keep out of reach of children. If swallowed,
get medical help or contact a Poison Control
Center right away.

Directions
For sunscreen use: • apply liberally 15
minutes before sun exposure • use a water
resistant sunscreen if swimming or sweating
• reapply at least every two hours
Children under 6 months of age: ask a doctor

Stop use and ask a doctor if rash occurs

Keep out of reach of children.

If swallowed, get medical help or contact a Poison Control Center right away.

Directions
For sunscreen use: • apply liberally 15
minutes before sun exposure • use a water
resistant sunscreen if swimming or sweating
• reapply at least every two hours
Children under 6 months of age: ask a doctor

Other information • protect this product
from excessive heat and direct sun.

Inactive ingredients Simmondsia chinensis
(Jojoba) Seed Oil, Heptyl Undecylenate,
Euphorbia cerifera (Candelilla) Wax, Prunus
amygdalus dulcis (Sweet Almond) Oil, Jojoba
Esters, Persea gratissima (Avocado) Oil,
Theobroma cacao (Cocoa) Seed Butter,
Butyloctyl Salicylate, Rubus idaeus (Raspberry)
Seed Oil, Butyrospermum parkii (Shea) Butter,
Daucus carota sativa (Carrot) Seed Oil,
Boswellia carterii (Frankincense) Oil,
Helichrysum italicum Flower/Leaf/Stem Oil,
Cocos nucifera (Coconut) Fruit Extract,
Helianthus annuus (Sunflower) Seed Oil,
Bisabolol, Cymbopogon flexuosus
(Lemongrass) Oil, Mentha spicata
(Spearmint) Leaf/Stem Oil, Leptospermum
scoparium (Manuka) Branch/Leaf Oil,
Schinziophyton rautanenii (Mongongo) Kernel
Oil, Stevia rebaudiana Leaf/Stem Extract,
Beta-Sitosterol, Squalene, Carthamus
tinctorius (Safflower) Seed Oil, Ricinus
communis (Castor) Seed Oil, Aloe
barbadensis (Aloe) Extract, Helianthus
annuus (Sunflower) Seed Wax, Honey,
Tocopherol, Sodium Hyaluronate, Citrus
nobilis (Mandarin Orange) Peel Oil